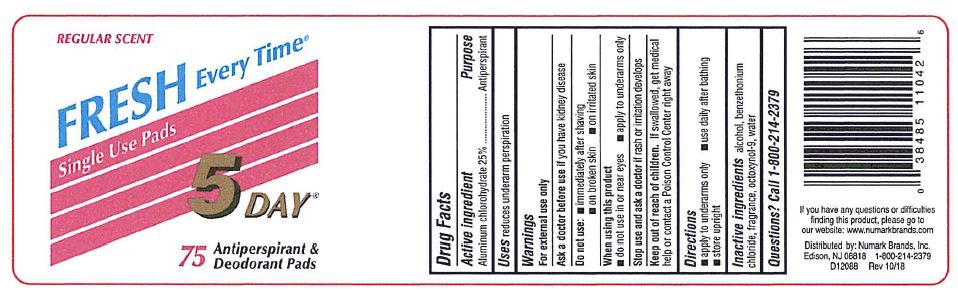 DRUG LABEL: 5 Day
NDC: 69846-110 | Form: LIQUID
Manufacturer: NUMARK BRANDS, INC
Category: otc | Type: HUMAN OTC DRUG LABEL
Date: 20251215

ACTIVE INGREDIENTS: Aluminum Chlorohydrate 0.25 g/1 1
INACTIVE INGREDIENTS: Alcohol; Benzethonium Chloride; Water

Drug Facts

ACTIVE INGREDIENT

Active ingredient | Purpose
Aluminum chlorohydrate 25% | Antiperspirant

INDICATIONS AND USAGE

Uses reduces underarm perspiration

Warnings

For external use only

Ask a doctor before use if you have kidney disease

Do not use

- immediately after shaving
- on broken skin
- on irritated skin

When using this product

- do not use in or near eyes
- apply to underarms only

Stop use and ask a doctor if rash or irritation develops

Keep out of reach of children. If swallowed, get medical help or contact a Poison Control Center right away

Directions

- apply to underarms only
- use daily after bathing
- store upright

INACTIVE INGREDIENT

Inactive ingredients alcohol, benzethonium chloride, fragrance, octoxynol-9, water

Questions? Call 1-800-214-2379

PRINCIPAL DISPLAY PANEL

REGULAR SCENT
FRESH EVERY TIME®
Single Use Pads
5 DAY®
75 Antiperspirant & Deodorant Pads
If you have any questions or difficulties
finding this product, please go to
our website: www.numarkbrands.com
Distributed by: Numark Brands, Inc.
Edison, NJ 08818 1-800-214-2379
D12088 Rev 10/18